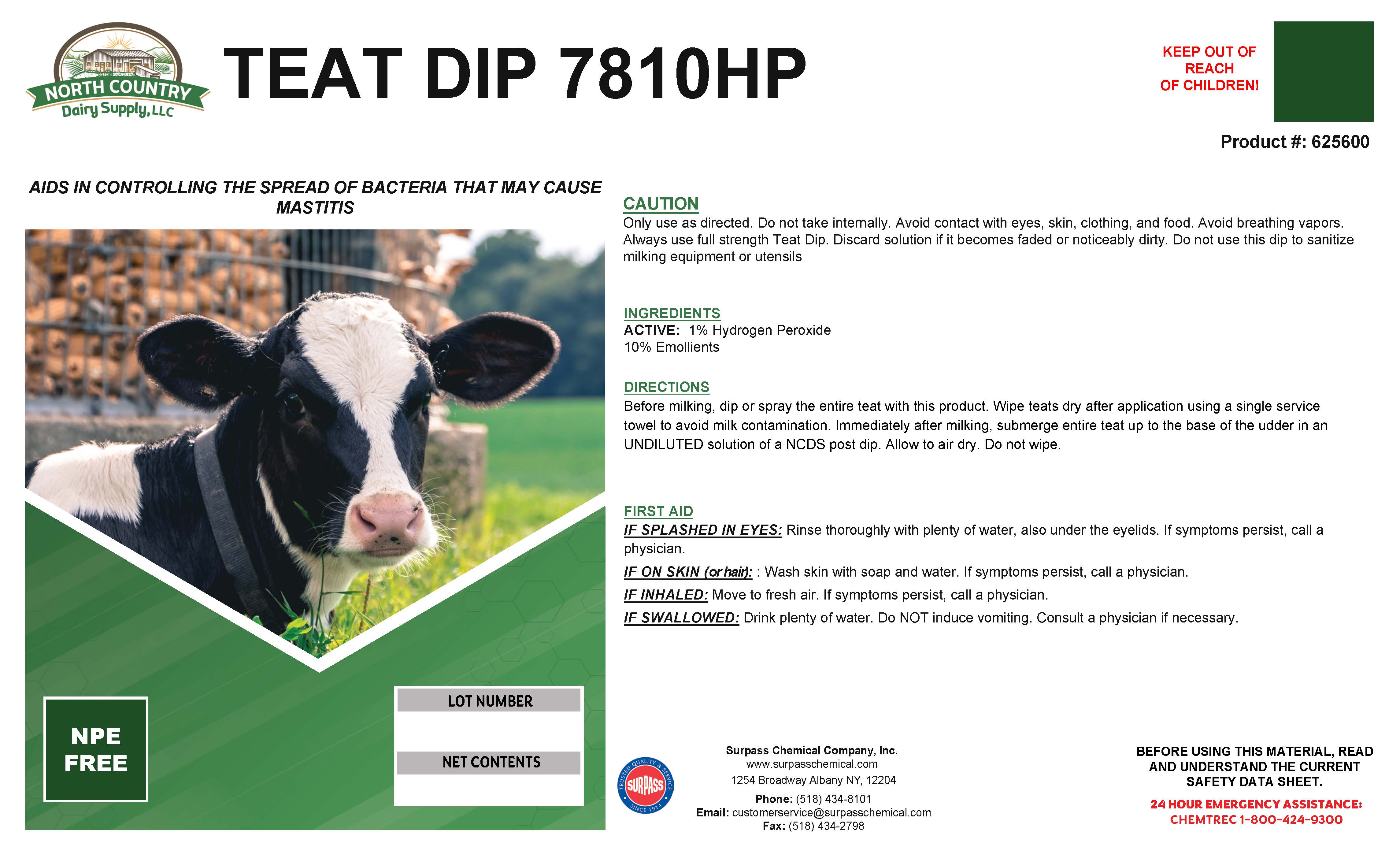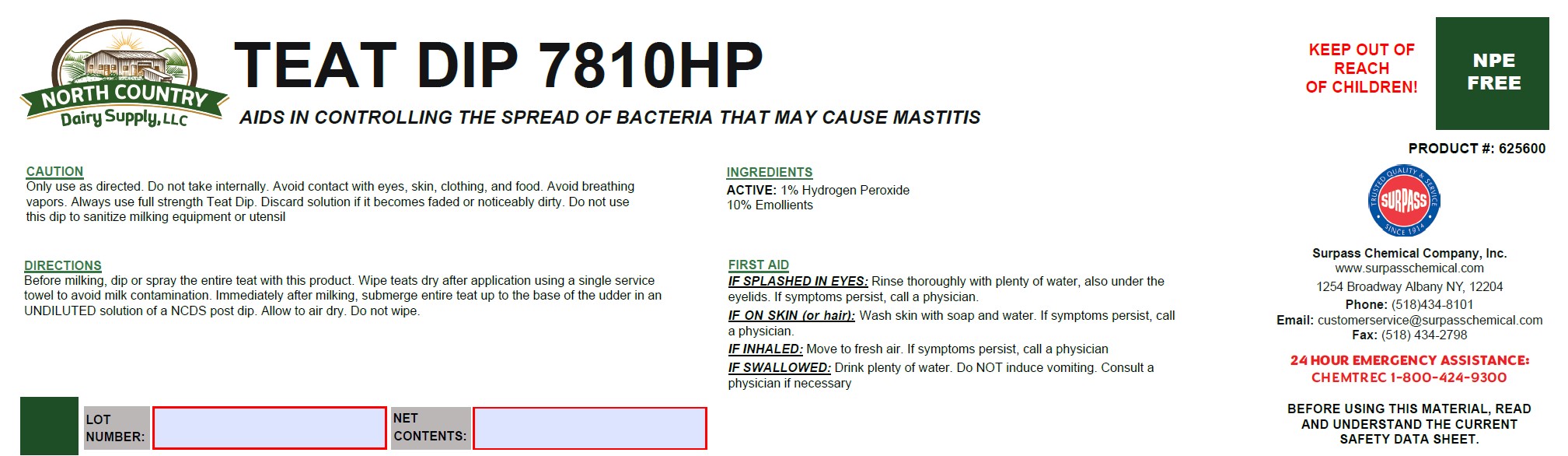 DRUG LABEL: Teat Dip 7810HP
NDC: 86067-0118 | Form: SOLUTION
Manufacturer: Surpass Chemical Company, Inc.
Category: animal | Type: OTC ANIMAL DRUG LABEL
Date: 20251229

ACTIVE INGREDIENTS: HYDROGEN PEROXIDE 0.03 kg/1 kg
INACTIVE INGREDIENTS: WATER 0.82498 kg/1 kg; GLYCERIN 0.1 kg/1 kg; LACTIC ACID 0.02 kg/1 kg; BENZENE 0.005 kg/1 kg; SODIUM C14-18 OLEFIN SULFONATE 0.01 kg/1 kg; C9-11 PARETH-3 0.01 kg/1 kg; METHYLENE BLUE 0.00001 kg/1 kg; FD&C YELLOW NO. 5 .00001 kg/1 kg

Teat Dip 7810HP

DIRECTIONS:
Before milking, dip or spray the entire teat with this product. Wipe teats dry after application using a single service towel to avoid milk contamination. Immediately after milking, submerge entire teat up to the base of the udder in an UNDILUTED solution of a NCDS post dip. Allow to air dry. Do not wipe.

DESCRIPTION

TEAT DIP 7810HP

An aid in a complete cow care program to help control external organisms that may cause mastitis. PRODUCT #: 625600

ACTIVE INGREDIENT

INGREDIENTS:
ACTIVE: 1% Hydrogen Peroxide

10% Emollients

OTHER SAFETY INFORMATION

FIRST AID:
IF SPLASHED IN EYES: Rinse thoroughly with plenty of water, also under the eyelids. If symptoms persist, call a physician.

IF ON SKIN (or hair): Wash skin with soap and water. If symptoms persist, call a physician.

IF INHALED: Move to fresh air. If symptoms persist, call a physician.

IF SWALLOWED: Drink plenty of water. Do NOT induce vomiting. Consult a physician if necessary

SAFE HANDLING WARNING

BEFORE USING THIS MATERIAL, READ AND
UNDERSTAND THE CURRENT SAFETY DATA SHEET.

Surpass Chemical Company, Inc.
www.surpasschemical.com
1254 Broadway Albany NY, 12204

Phone: (518) 434-8101

Email: customerservice@surpasschemical.com

Fax: (518) 434-2798

KEEP OUT OF REACH OF CHILDREN!